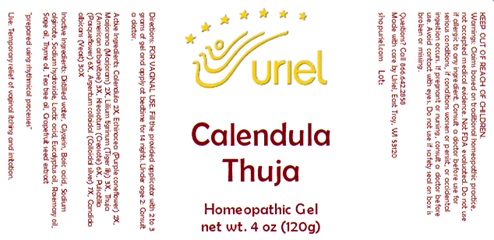 DRUG LABEL: Calendula Thuja
NDC: 48951-3267 | Form: GEL
Manufacturer: Uriel Pharmacy Inc.
Category: homeopathic | Type: HUMAN OTC DRUG LABEL
Date: 20240411

ACTIVE INGREDIENTS: CALENDULA OFFICINALIS FLOWERING TOP 2 [hp_X]/1 g; ECHINACEA, UNSPECIFIED 2 [hp_X]/1 g; ORIGANUM MAJORANA WHOLE 2 [hp_X]/1 g; LILIUM LANCIFOLIUM WHOLE FLOWERING 3 [hp_X]/1 g; THUJA OCCIDENTALIS WHOLE 3 [hp_X]/1 g; WOOD CREOSOTE 6 [hp_X]/1 g; PULSATILLA VULGARIS 6 [hp_X]/1 g; SILVER 7 [hp_X]/1 g; CANDIDA ALBICANS 30 [hp_X]/1 g
INACTIVE INGREDIENTS: BORIC ACID; CITRUS PARADISI SEED; TEA TREE OIL; WATER; GLYCERIN; SODIUM ALGINATE; LACTIC ACID; EUCALYPTUS OIL; ROSEMARY OIL; SAGE OIL; THYME OIL; SODIUM HYDROXIDE

Calendula Thuja

INDICATIONS AND USAGE

Directions: FOR VAGINAL USE

DOSAGE AND ADMINISTRATION

Fill the provided applicator with 2 to 3 grams of gel and apply at bedtime for 14 nights.

ACTIVE INGREDIENT

Active Ingredients: Calendula 2X, Echinacea (Purple coneflower) 2X, Marjorana (Marjoram) 2X, Lilium tigrinum (Tiger lily) 3X, Thuja (American arborvitae) 3X, Kreosotum (Creosote) 6X, Pulsatilla (Pasqueflower) 6X, Argentum colloidal (Colloidal silver) 7X, Candida albicans (Yeast) 30X

INACTIVE INGREDIENT

Inactive Ingredients: Distilled water, Glycerin, Boric acid, Sodium alginate, Sodium hydroxide, Lactic acid, Eucalyptus oil, Rosemary oil, Sage oil, Thyme oil, Tea tree oil, Grapefruit seed extract

"prepared using rhythmical processes"

PURPOSE

Use: Temporary relief of vaginal itching and irritation.

KEEP OUT OF REACH OF CHILDREN.

WARNINGS

Warnings: Claims based on traditional homeopathic practice, not accepted medical evidence. Not FDA evaluated. Do not use if allergic to any ingredient. Consult a doctor before use for serious conditions, if conditions worsen or persist, or accidental ingestion occurs. If pregnant or nursing consult a doctor before use. Avoid contact with eyes. Do not use if safety seals on box are broken or missing. BEST WHEN USED WITHIN 30 DAYS OF OPENING.

QUESTIONS

Questions? Call 866.642.2858 Made with care by Uriel, East Troy, WI 53120 shopuriel.com Lot: